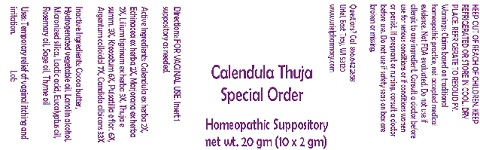 DRUG LABEL: Calendula Thuja Adult Size
NDC: 48951-3168 | Form: SUPPOSITORY
Manufacturer: Uriel Pharmacy Inc.
Category: homeopathic | Type: HUMAN OTC DRUG LABEL
Date: 20180423

ACTIVE INGREDIENTS: CALENDULA OFFICINALIS FLOWERING TOP 2 [hp_X]/1 g; ECHINACEA, UNSPECIFIED 2 [hp_X]/1 g; SWEET MARJORAM 2 [hp_X]/1 g; LILIUM LANCIFOLIUM WHOLE FLOWERING 3 [hp_X]/1 g; THUJA OCCIDENTALIS WHOLE 3 [hp_X]/1 g; WOOD CREOSOTE 6 [hp_X]/1 g; PULSATILLA VULGARIS 6 [hp_X]/1 g; SILVER 7 [hp_X]/1 g; CANDIDA ALBICANS 33 [hp_X]/1 g
INACTIVE INGREDIENTS: COCOA BUTTER; CORN OIL; LANOLIN ALCOHOLS; SILICON DIOXIDE; LACTIC ACID; EUCALYPTUS OIL; ROSEMARY OIL; SAGE OIL; THYME OIL

Calendula Thuja Adult Size

INDICATIONS AND USAGE

Directions: FOR VAGINAL USE.

DOSAGE AND ADMINISTRATION

Insert 1 suppository as needed.

ACTIVE INGREDIENT

Active Ingredients: Calendula ex herba 2X, Echinacea ex herba 2X, Marjorana ex herba 2X, Lilium tigrinum ex herba 3X, Thuja e summ. 3X, Kreosotum 6X, Pulsatilla e flor. 6X, Argentum colloidal 7X, Candida albicans 33X

INACTIVE INGREDIENT

Inactive Ingredients: Cocoa butter, Hydrogenated vegetable oil, Lanolin alcohol, Micronized silica, Lactic acid, Eucalyptus oil, Rosemary oil, Sage oil, Thyme oil

PURPOSE

Uses: Temporary relief of vaginal itching and irritation.

KEEP OUT OF REACH OF CHILDREN.

WARNINGS

KEEP REFRIGERATED OR STORE IN COOL, DRY PLACE. REFRIGERATE TO RESOLIDIFY.
Warnings: Claims based on traditional homeopathic practice, not accepted medical evidence. Not FDA evaluated. Do not use if allergic to any ingredient. Consult a doctor before use for serious conditions or if conditions worsen or persist. If pregnant or nursing, consult a doctor before use. Do not use if safety seals on box are broken or missing.

QUESTIONS

Questions? Call 866.642.2858 Uriel, East Troy, WI 53120 www.urielpharmacy.com